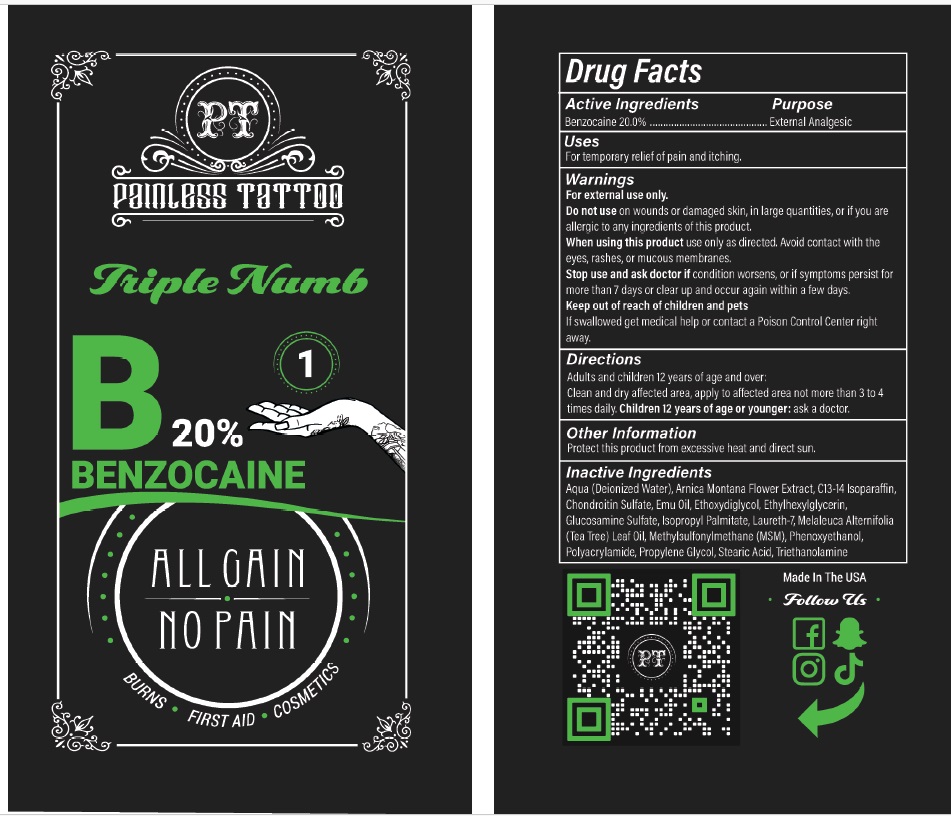 DRUG LABEL: Painless Tattoo 1
NDC: 54723-015 | Form: CREAM
Manufacturer: Sambria Pharmaceuticals, LLC
Category: otc | Type: HUMAN OTC DRUG LABEL
Date: 20251112

ACTIVE INGREDIENTS: BENZOCAINE 20 g/100 mL
INACTIVE INGREDIENTS: WATER; ARNICA MONTANA FLOWER; C13-14 ISOPARAFFIN; CHONDROITIN SULFATE (BOVINE); EMU OIL; DIETHYLENE GLYCOL MONOETHYL ETHER; ETHYLHEXYLGLYCERIN; GLUCOSAMINE SULFATE; ISOPROPYL PALMITATE; LAURETH-7; TEA TREE OIL; DIMETHYL SULFONE; PHENOXYETHANOL; POLYACRYLAMIDE (CROSSLINKED; 2 MOLE PERCENT BISACRYLAMIDE); PROPYLENE GLYCOL; STEARIC ACID; TROLAMINE

Active ingredient

Benzocaine 20%

Purpose

External Analgesic

Uses

For temporary relief of pain and itching.

Warnings

For external use only.

Do not use onwounds or damaged skin, in large quantities, or if you are allergic to any ingredients of this product.

When using this productuse only as directed. Avoid contact with the eyes, rashes, or mucous membranes.

Stop use and ask doctor ifcondition worsens, or if symptoms persist for more than 7 days or clear up and occur again within a few days.

Keep out of reach of children and petsIf swallowed get medical help or contact a Poison Control Center right away.

Directions

Adults and children 12 years of age and over:
Clean and dry affected area, apply to affected area not more than 3 to 4 times daily.

Children 12 years of age or younger: ask a doctor.

Other Information

Protect this product from excessive heat and direct sun.

Inactive ingredients

Aqua (Deionized Water), Arnica Montana Flower Extract, C13-14 Isoparaffin, Chondroitin Sulfate, Emu Oil, Ethoxydiglycol, Ethylhexylglycerin, Glucosamine Sulfate, Isopropyl Palmitate, Laureth-7, Melaleuca Alternifolia (Tea Tree) Leaf Oil, Methylsulfonylmethane (MSM), Phenoxyethanol, Polyacrylamide, Propylene Glycol, Stearic Acid, Triethanolamine